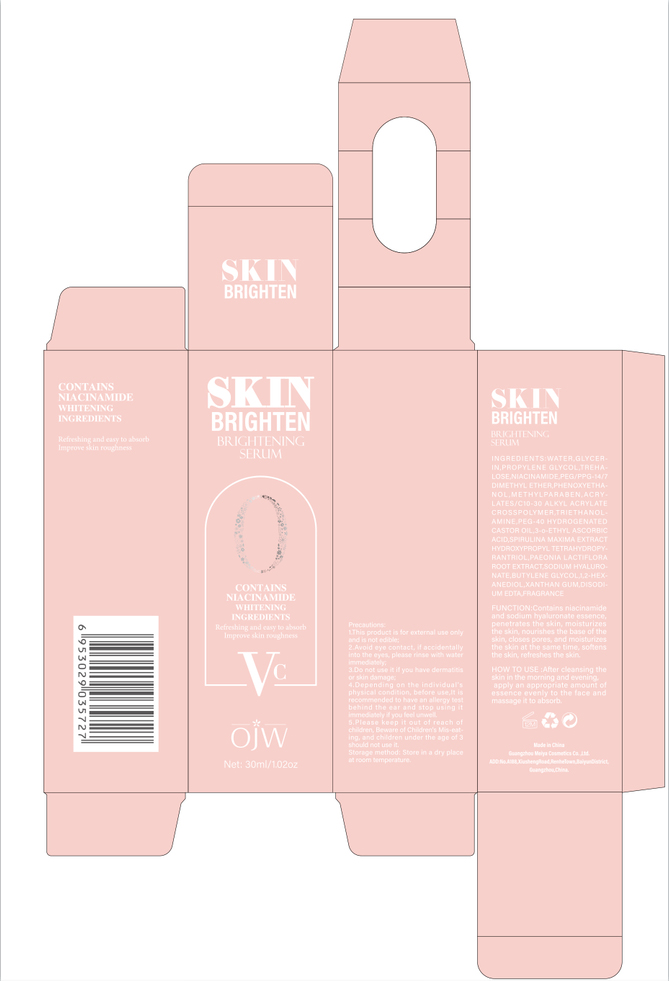 DRUG LABEL: whitening
NDC: 84673-003 | Form: EMULSION
Manufacturer: Guangzhou Meiya Cosmetics Co.. Ltd.
Category: otc | Type: HUMAN OTC DRUG LABEL
Date: 20240917

ACTIVE INGREDIENTS: NIACINAMIDE 2 g/1 mg; 3-O-ETHYL ASCORBIC ACID 0.15 g/1 mg
INACTIVE INGREDIENTS: BUTYLENE GLYCOL 0.01 g/1 mg; GLYCERIN 5 g/1 mg; WATER 84.9 g/1 mg; METHYLPARABEN 0.35 g/1 mg; 1,2-HEXANEDIOL 1 g/1 mg; PHENOXYETHANOL 0.5 g/1 mg; PEG/PPG-14/7 DIMETHYL ETHER 1 g/1 mg; TREHALOSE 2 g/1 mg; ACRYLATES/C10-30 ALKYL ACRYLATE CROSSPOLYMER (60000 MPA.S AT 0.5%) 0.25 g/1 mg; XANTHAN GUM 0.1 g/1 mg; HYDROXYPROPYL TETRAHYDROPYRANTRIOL 0.1 g/1 mg

ACTIVE INGREDIENT

NIACINAMIDE 2%
3-o-ETHYL ASCORBIC ACID 0.15%

PURPOSE

Function:Contains niacinamide and sodium hyaluronate essence, penetrates the skin, moisturizes the skin, nourishes the base of the skin, closes pores, and moisturizes the skin at the same time, softens the skin, refreshes the skin.

INDICATIONS AND USAGE

HOW TO USE :After cleansing the skin in the morning and evening,

apply an appropriate amount of essence evenly to the face and massage it to absorb.

WARNINGS

Precautions:

1. This product is for external use only and is not edible;

2. Avoid eye contact, if accidentally into the eyes, please rinse with water immediately;

3. Do not use it if you have dermatitis or skin damage;

4. Depending on the individual's physical condition, before use,It is recommended to have an allergy test behind the ear and stop using it immediately if you feel unwell.

5. Please keep it out of reach of children, Beware of Children's Mis-eating, and children under the age of 3 should not use it.
6.Store in a dry place at room temperature.

STOP USE

1. Avoid eye contact, if accidentally into the eyes, please rinse with water immediately;

2. Do not use it if you have dermatitis or skin damage;

3. Depending on the individual's physical condition, before use,It is recommended to have an allergy test behind the ear and stop using it immediately if you feel unwell.

DO NOT USE

1. Avoid eye contact, if accidentally into the eyes, please rinse with water immediately;

2. Do not use it if you have dermatitis or skin damage;

3. Depending on the individual's physical condition, before use,It is recommended to have an allergy test behind the ear and stop using it immediately if you feel unwell.

KEEP OUT OF REACH OF CHILDREN

Please keep it out of reach of children, Beware of Children's Mis-eating, and children under the age of 3 should not use it.

WHEN USING

1. This product is for external use only and is not edible;

2. Avoid eye contact, if accidentally into the eyes, please rinse with water immediately;

3. Do not use it if you have dermatitis or skin damage;

4. Depending on the individual's physical condition, before use,It is recommended to have an allergy test behind the ear and stop using it immediately if you feel unwell.

5. Please keep it out of reach of children, Beware of Children's Mis-eating, and children under the age of 3 should not use it.
6.Store in a dry place at room temperature.

DOSAGE AND ADMINISTRATION

After cleansing the skin in the morning and evening,

apply an appropriate amount of essence evenly to the face and massage it to absorb.